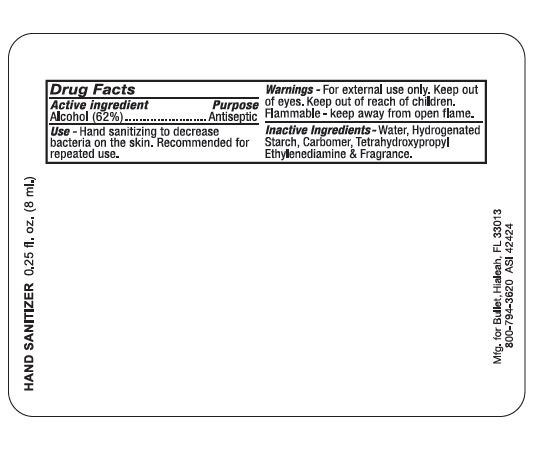 DRUG LABEL: Hand Sanitizer
NDC: 19392-110 | Form: LIQUID
Manufacturer: Bullet Line, LLC
Category: otc | Type: HUMAN OTC DRUG LABEL
Date: 20200624

ACTIVE INGREDIENTS: ALCOHOL 620 mL/1000 mL
INACTIVE INGREDIENTS: WATER; CARBOMER HOMOPOLYMER TYPE C (ALLYL PENTAERYTHRITOL CROSSLINKED); ETHYLENEDIAMINE CARBAMATE; HYDROGENATED STARCH HYDROLYSATE

Drug Facts

ACTIVE INGREDIENT

Alcohol (62%)

PURPOSE

Antiseptic

Keep out of reach of children

INDICATIONS AND USAGE

For hand sanitizing to decrease bacteria on the skin. Recommended for repeated use.

WARNINGS

For external use only

Do not use in or near the eyes

Stop use and ask a doctor if irritation or rash appears and lasts

Keep out of reach of children

If swallowed, contact a doctor or Poison Control Center right away.

DOSAGE AND ADMINISTRATION

Wet hands thoroughly with product and allow to dry without wiping

INACTIVE INGREDIENT

Water, Hydrogenated starch, Carbomer, Tetrahydroxypropyl Ethylenediamine, Fragrance